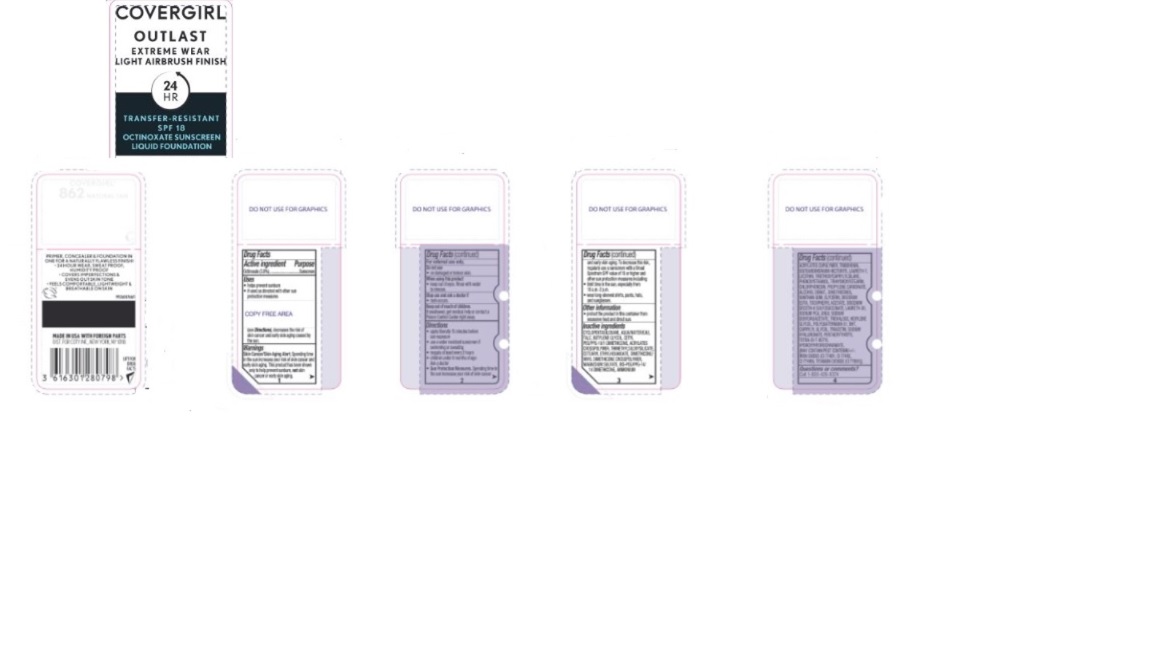 DRUG LABEL: Covergirl Outlast Extreme Wear 3-in-1 Foundation 24 HR Full Coverage SPF 18 Octinoxate Sunscreen Liquid Foundation
NDC: 22700-030 | Form: EMULSION
Manufacturer: Noxell Corporation
Category: otc | Type: HUMAN OTC DRUG LABEL
Date: 20241121

ACTIVE INGREDIENTS: OCTINOXATE 30 mg/1 mL
INACTIVE INGREDIENTS: BUTYLENE GLYCOL; HEXYLENE GLYCOL; GLYCERIN; (4-NITROPHENYL)UREA; TRIETHOXYCAPRYLYLSILANE; CETEARYL ETHYLHEXANOATE; SODIUM HYALURONATE; LAURETH-30; TREHALOSE; BHT; CHLORPHENESIN; SODIUM DEHYDROACETATE; SODIUM PCA; LAURETH-7; TALC; TRIBEHENIN; IRON OXIDES; TRIHYDROXYSTEARIN; DISTEARDIMONIUM HECTORITE; MAGNESIUM SULFATE; BIS-PEG/PPG-14/14 DIMETHICONE; CAPRYLYL GLYCOL; TRIACETIN; PENTAERYTHRITYL TETRA-DI-T-BUTYL HYDROXYHYDROCINNAMATE; PHENOXYETHANOL; PROPYLENE CARBONATE; XANTHAN GUM; DISODIUM DECETH-6 SULFOSUCCINATE; CYCLOPENTASILOXANE

Active Ingredients

Octinoxate 3.0%

Purpose

Sunscreen

Uses

- helps prevent sunburn
- if used as directed with other sun protection measures

(see Directions), decreases the risk of skin cancer and early aging caused by the sun.

Warnings

Skin Cancer/Skin Aging Alert; ;Spending time inthesunincreasesyourriskofskincancerand earlyskinaging.Thisproducthasbeenshown only to help prevent sunburn, not skin cancer or early skin aging.

For external use only.

Do not use

- on damaged or broken skin.

When using this product

- keep out of eyes. Rinse with water to remove.

Stop use and ask doctor if

- rash occurs.

Keep out of reach of children.

If swollowed, get medical help or contact a Poison Control Center right away.

Directions

- apply liberally 15 minutes before sun exposure
- useawaterresistantsunscreenif swimming or sweating
- reapply at least every 2 hours
- children under 6 months of age: Ask a doctor
- Sun Protection Measures.Spending time in the sun increases your risk of skin cancer and early skin aging. To decrease this risk, regularly use a sunscreen witha Broad SpectrumSPF valueof 15 or higher and other sun protection measures including:
- limit time in the sun,especially from 10 a.m.-2 p.m.
- wear long-sleeved shirts, pants, hats, and sunglasses.

Other information

- protect the product in this container from excessive heat and direct sun.

Inactive ingredients

CYCLOPENTASILOXANE, AQUA/WATER/EAU, TALC, BUTYLENE GLYCOL, CETYL PEG/PPG-10/1 DIMETHICONE, ACRYLATES CROSSPOLYMER, TRIMETHYLSILOXYSILICATE, CETEARYL ETHYLHEXANOATE, DIMETHICONE/ VINYL DIMETHICONE CROSSPOLYMER, MAGNESIUM SULFATE, BIS-PEG/PPG-14/ 14 DIMETHICONE, AMMONIUM

ACRYLATES COPOLYMER, TRIBEHENIN, DISTEARDIMONIUM HECTORITE, LAURETH-7, LECITHIN, TRIETHOXYCAPRYLYLSILANE, PHENOXYETHANOL, TRIHYDROXYSTEARIN, CHLORPHENESIN, PROPYLENE CARBONATE, ALCOHOL DENAT., DIMETHICONOL, XANTHAN GUM, GLYCERIN, DISODIUM EDTA, TOCOPHERYL ACETATE, DISODIUM DECETH-6 SULFOSUCCINATE, LAURETH-30, SODIUM PCA, UREA, SODIUM DEHYDROACETATE, TREHALOSE, HEXYLENE GLYCOL, POLYQUATERNIUM-51, BHT, CAPRYLYL GLYCOL, TRIACETIN, SODIUM HYALURONATE, PENTAERYTHRITYL TETRA-DI-T-BUTYL HYDROXYHYDROCINNAMATE, [MAY CONTAIN/PEUT CONTENIR/+/-: IRON OXIDES (CI 77491, CI 77492, CI 77499), TITANIUM DIOXIDE (CI 77891)].

Questions or comments?

Call 1-800-426-8374